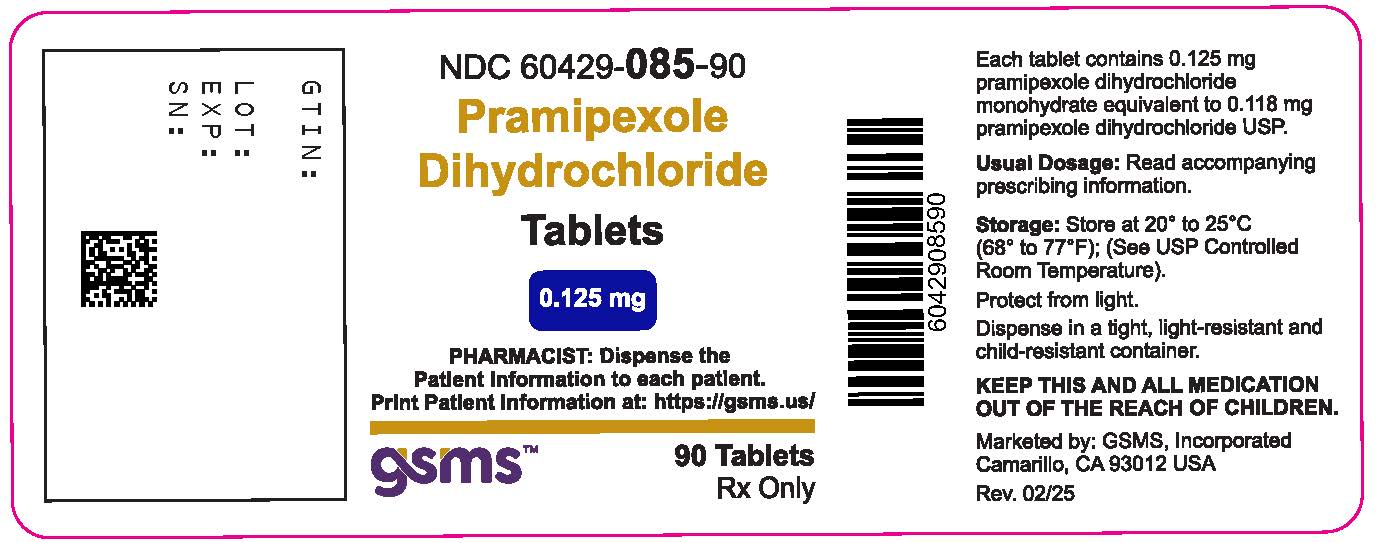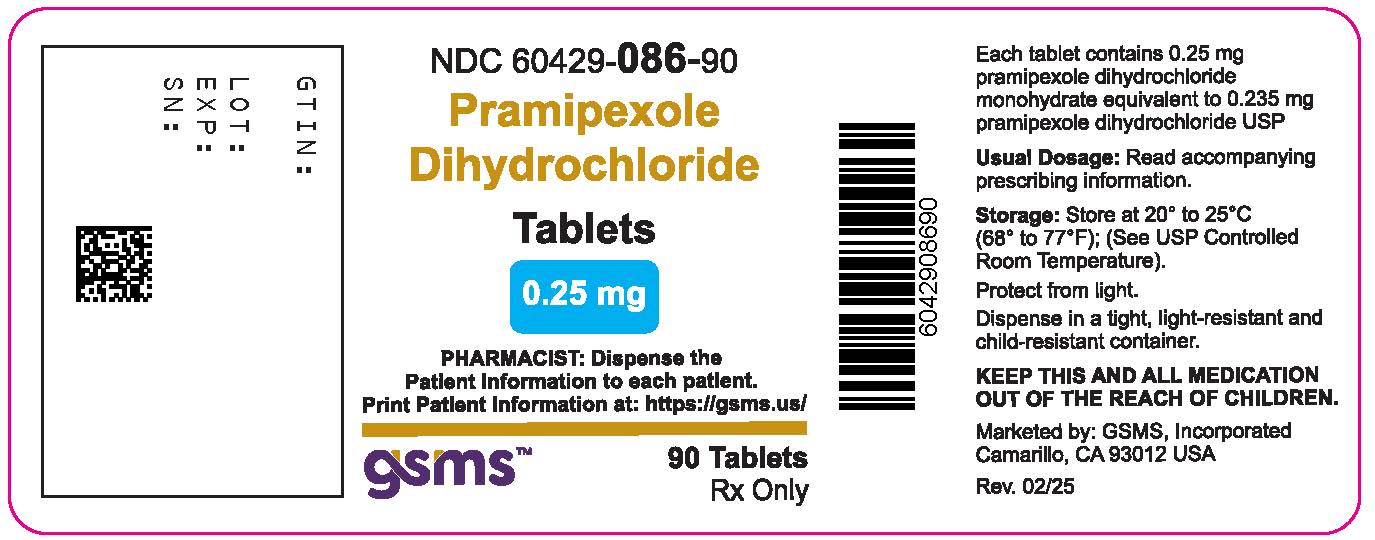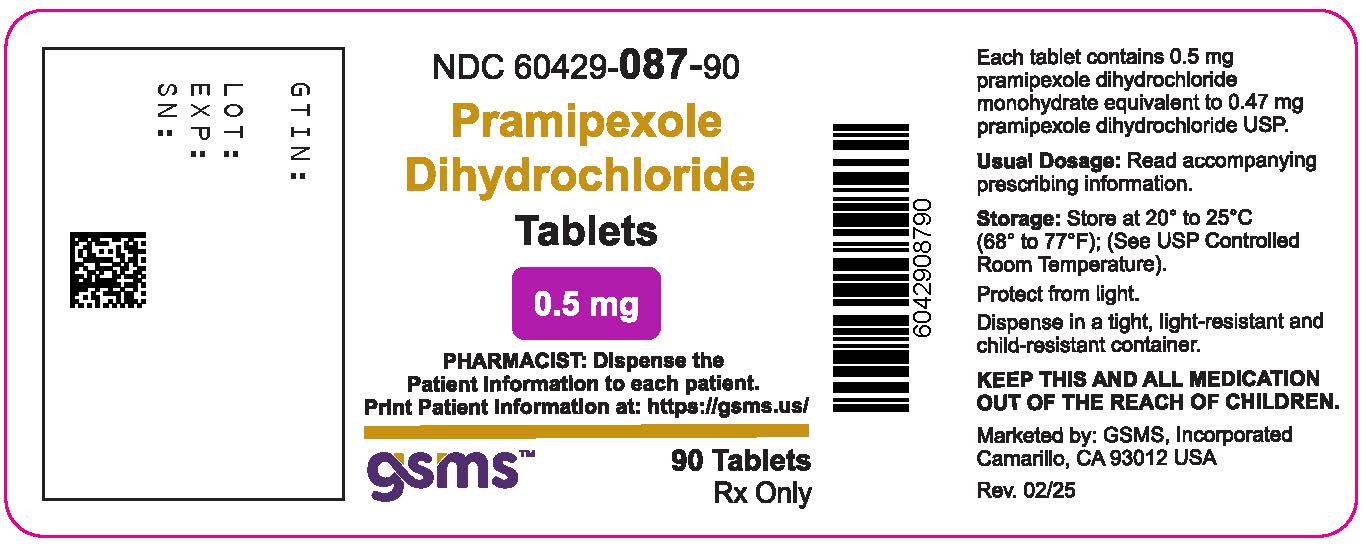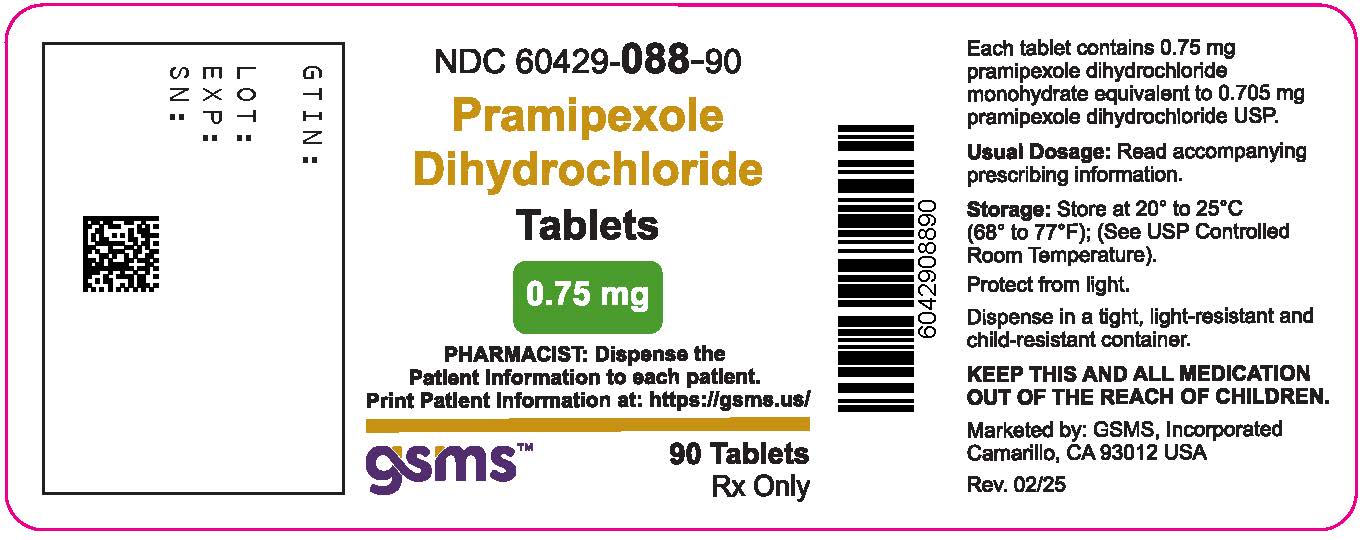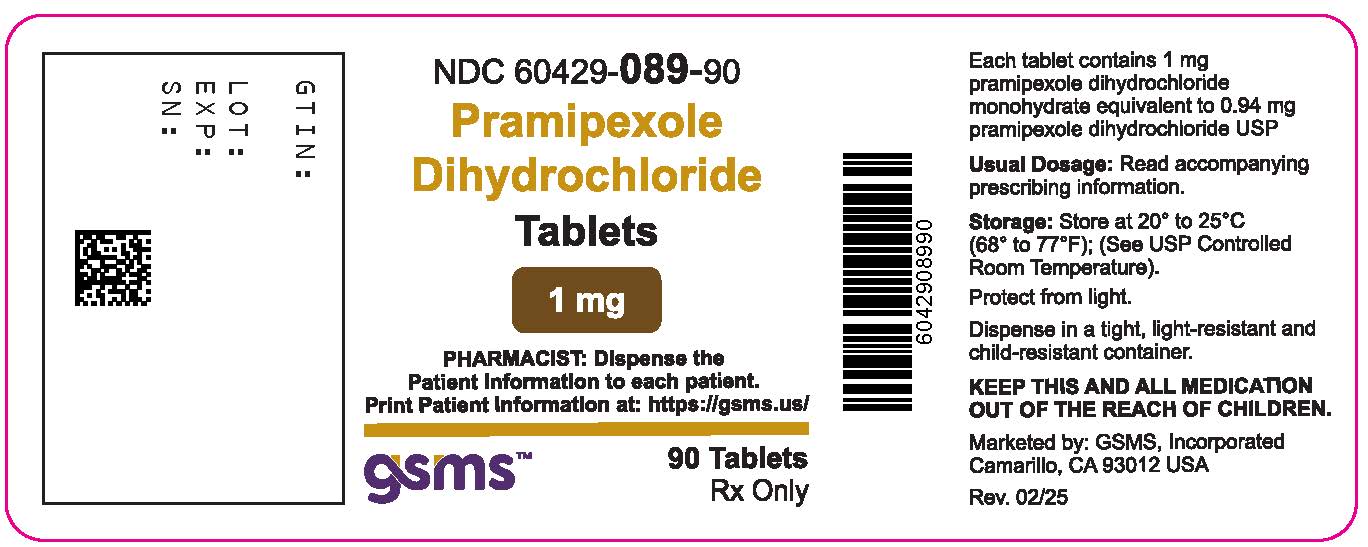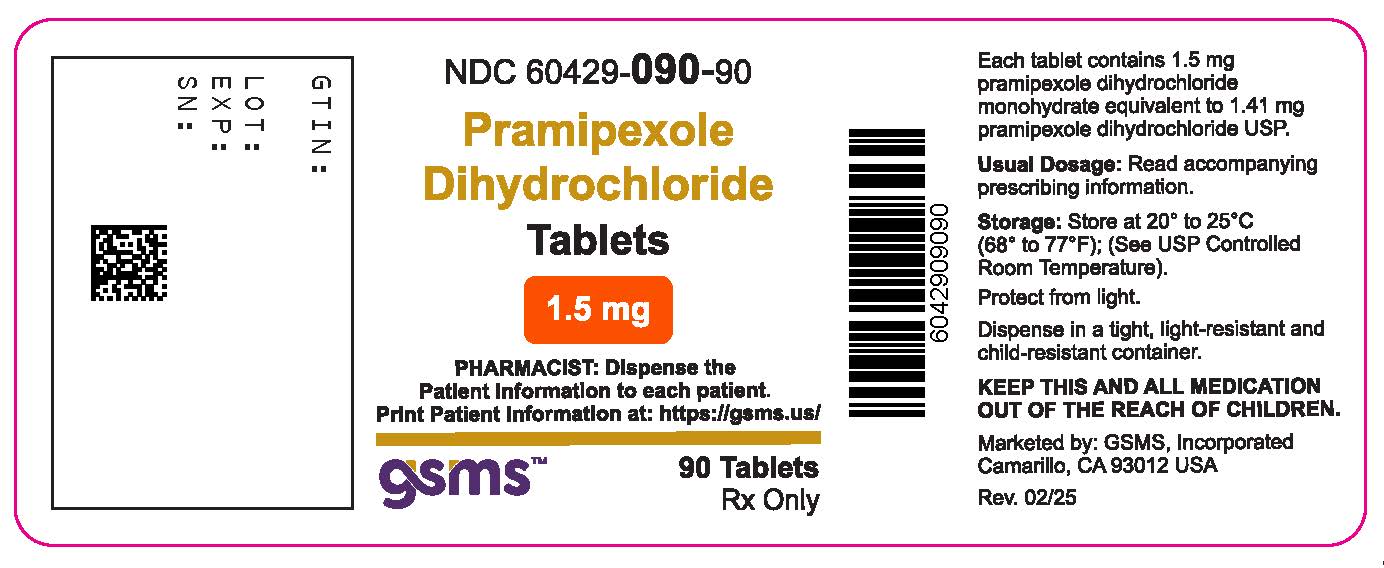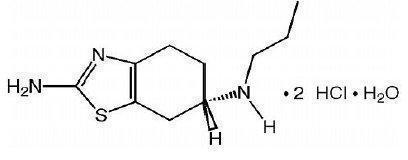 DRUG LABEL: Pramipexole Dihydrochloride
NDC: 60429-085 | Form: TABLET
Manufacturer: Golden State Medical Supply, Inc.
Category: prescription | Type: HUMAN PRESCRIPTION DRUG LABEL
Date: 20260126

ACTIVE INGREDIENTS: PRAMIPEXOLE DIHYDROCHLORIDE 0.125 mg/1 1
INACTIVE INGREDIENTS: SILICON DIOXIDE; STARCH, CORN; MAGNESIUM STEARATE; MANNITOL; POVIDONE, UNSPECIFIED

HIGHLIGHTS OF PRESCRIBING INFORMATION

PRAMIPEXOLE DIHYDROCHLORIDE TABLETS. These highlights do not include all the information needed to use PRAMIPEXOLE DIHYDROCHLORIDE TABLETS safely and effectively. See full prescribing information for PRAMIPEXOLE DIHYDROCHLORIDE TABLETS.
PRAMIPEXOLE DIHYDROCHLORIDE tablets, for oral use
Initial U.S. Approval: 1997

RECENT MAJOR CHANGES

Warnings and Precautions, Withdrawal Symptoms (5.11) | 7/2021

1 INDICATIONS AND USAGE

PRAMIPEXOLE DIHYDROCHLORIDE tablets are a non-ergot dopamine agonist indicated for the treatment of:

- Parkinson’s disease (PD) (1.1)
- Moderate-to-severe primary Restless Legs Syndrome (RLS) (1.2)

2 DOSAGE AND ADMINISTRATION

Parkinson’s Disease-Normal Renal Function* (2.2)
Week | Dosage (mg) | Total Daily Dose (mg)
1 | 0.125 TID | 0.375
2 | 0.25 TID | 0.75
3 | 0.5 TID | 1.5
4 | 0.75 TID | 2.25
5 | 1 TID | 3
6 | 1.25 TID | 3.75
7 | 1.5 TID | 4.5
* Doses should not be increased more frequently than every 5-7 days. Titrate to effective dose. If used with levodopa, may need to reduce levodopa dose.

Parkinson’s Disease-Impaired Renal Function (2.2)
Creatinine Clearance | Starting Dose (mg) | Maximum Dose (mg)
> 50 mL/min | 0.125 TID | 1.5 TID
30 to 50 mL/min | 0.125 BID | 0.75 TID
15 to 30 mL/min | 0.125 QD | 1.5 QD
< 15 mL/min and hemodialysis patients |  | Data not available

Restless Legs Syndrome*(2.3)
Titration Step | Dose (mg) 2-3 hours before bedtime
1 | 0.125
2 (if needed) | 0.25
3 (if needed) | 0.5
*Dosing interval is 4-7 days (14 days in patients with CrCl 20-60 mL/min)

3 DOSAGE FORMS AND STRENGTHS

Tablets: 0.125 mg, 0.25 mg (functional scored tablets), 0.5 mg (functional scored tablets), 0.75 mg, 1 mg (functional scored tablets), and 1.5 mg (functional scored tablets) (3).

4 CONTRAINDICATIONS

None (4)

5 WARNINGS AND PRECAUTIONS

- Falling Asleep During Activities of Daily Living: Sudden onset of sleep may occur without warning; advise patients to report symptoms (5.1)
- Symptomatic Orthostatic Hypotension: Monitor during dose escalation (5.2)
- Impulse Control/Compulsive Behaviors: Patients may experience compulsive behaviors and other intense urges (5.3)
- Hallucinations and Psychotic-like Behavior: May occur; risk increases with age. (5.4)
- Dyskinesia: May be caused or exacerbated by PRAMIPEXOLE DIHYDROCHLORIDE tablets (5.5)
- Postural Deformity: Consider reducing the dose or discontinuing PRAMIPEXOLE DIHYDROCHLORIDE tablets if postural deformity occurs (5.6)

6 ADVERSE REACTIONS

Most common adverse reactions (incidence >5% and greater than placebo):

- Early PD without levodopa: nausea, dizziness, somnolence, insomnia, constipation, asthenia, and hallucinations (6.1)
- Advanced PD with levodopa: postural (orthostatic) hypotension, dyskinesia, extrapyramidal syndrome, insomnia, dizziness, hallucinations, accidental injury, dream abnormalities, confusion, constipation, asthenia, somnolence, dystonia, gait abnormality, hypertonia, dry mouth, amnesia, and urinary frequency (6.1)
- RLS: nausea, somnolence, fatigue, and headache (6.1)

To report SUSPECTED ADVERSE REACTIONS, contact ScieGen Pharmaceuticals, Inc. at 1-855-724-3436 or FDA at 1-800-FDA-1088 or www.fda.gov/medwatch.

7 DRUG INTERACTIONS

Dopamine antagonists: May diminish the effectiveness of pramipexole (7.1).

8 USE IN SPECIFIC POPULATIONS

Pregnancy: Based on animal data, may cause fetal harm (8.1).

FULL PRESCRIBING INFORMATION

1 INDICATIONS AND USAGE

1.1 Parkinson’s Disease

Pramipexole dihydrochloride tablets are indicated for the treatment of Parkinson’s disease.

1.2 Restless Legs Syndrome

Pramipexole dihydrochloride tablets are indicated for the treatment of moderate-to-severe primary Restless Legs Syndrome (RLS).

2 DOSAGE AND ADMINISTRATION

DOSAGE AND ADMINISTRATION

2.1 General Dosing Considerations

Pramipexole dihydrochloride tablets are taken orally, with or without food.

If a significant interruption in therapy with pramipexole dihydrochloride tablets has occurred, re-titration of therapy may be warranted.

2.2 Dosing for Parkinson’s Disease

In all clinical studies, dosage was initiated at a subtherapeutic level to avoid intolerable adverse effects and orthostatic hypotension. Pramipexole dihydrochloride tablets should be titrated gradually in all patients. The dose should be increased to achieve a maximum therapeutic effect, balanced against the principal side effects of dyskinesia, hallucinations, somnolence, and dry mouth.

Dosing in Patients with Normal Renal Function

Initial Treatment
Doses should be increased gradually from a starting dose of 0.375 mg/day given in three divided doses and should not be increased more frequently than every 5 to 7 days. A suggested ascending dosage schedule that was used in clinical studies is shown in Table 1:

Table 1 Ascending Dosage Schedule of Pramipexole Dihydrochloride Tablets for Parkinson’s Disease
Week | Dosage (mg) | Total Daily Dose (mg)
1 | 0.125 three times a day | 0.375
2 | 0.25 three times a day | 0.75
3 | 0.5 three times a day | 1.50
4 | 0.75 three times a day | 2.25
5 | 1 three times a day | 3.0
6 | 1.25 three times a day | 3.75
7 | 1.5 three times a day | 4.50

Maintenance Treatment
Pramipexole dihydrochloride tablets were effective and well tolerated over a dosage range of 1.5 to 4.5 mg/day administered in equally divided doses three times per day with or without concomitant levodopa (approximately 800 mg/day).

In a fixed-dose study in early Parkinson’s disease patients, doses of 3 mg, 4.5 mg, and 6 mg per day of pramipexole dihydrochloride tablets were not shown to provide any significant benefit beyond that achieved at a daily dose of 1.5 mg/day. However, in the same fixed-dose study, the following adverse events were dose related: postural hypotension, nausea, constipation, somnolence, and amnesia. The frequency of these events was generally 2-fold greater than placebo for pramipexole doses greater than 3 mg/day. The incidence of somnolence reported with pramipexole at a dose of 1.5 mg/day was comparable to placebo.

When pramipexole dihydrochloride tablets are used in combination with levodopa, a reduction of the levodopa dosage should be considered. In a controlled study in advanced Parkinson’s disease, the dosage of levodopa was reduced by an average of 27% from baseline.

Dosing in Patients with Renal Impairment

The recommended dosing of pramipexole dihydrochloride tablets in Parkinson’s disease patients with renal impairment is provided in Table 2.

Table 2 Dosing of Pramipexole Dihydrochloride Tablets in Parkinson’s Disease Patients with Renal Impairment
Renal Status | Starting Dose (mg) | Maximum Dose (mg)
Normal to mild impairment (creatinine Cl >50 mL/min) | 0.125 three times a day | 1.5 three times a day
Moderate impairment (creatinine Cl =30 to 50 mL/min) | 0.125 twice a day | 0.75 three times a day
Severe impairment (creatinine Cl =15 to <30 mL/min) | 0.125 once a day | 1.5 once a day
Very severe impairment (creatinine Cl <15 mL/min and hemodialysis patients) | The use of pramipexole dihydrochloride tablets has not been adequately studied in this group of patients.

Discontinuation of Treatment
Pramipexole dihydrochloride tablets may be tapered off at a rate of 0.75 mg per day until the daily dose has been reduced to 0.75 mg. Thereafter, the dose may be reduced by 0.375 mg per day [ see Warnings and Precautions(5.10) (5.11) ].

2.3 Dosing for Restless Legs Syndrome

The recommended starting dose of pramipexole dihydrochloride tablets is 0.125 mg taken once daily 2 to 3 hours before bedtime. For patients requiring additional symptomatic relief, the dose may be increased every 4 to 7 days (Table 3). Although the dose of pramipexole dihydrochloride tablets was increased to 0.75 mg in some patients during long-term open-label treatment, there is no evidence that the 0.75 mg dose provides additional benefit beyond the 0.5 mg dose.

Table 3 Ascending Dosage Schedule of Pramipexole Dihydrochloride tablets for RLS
Titration Step | Duration | Dose (mg) to be taken once daily, 2-3 hours before bedtime
1 | 4-7 days | 0.125
2* | 4-7 days | 0.25
3* | 4-7 days | 0.5

*if needed

Dosing in Patients with Renal Impairment
The duration between titration steps should be increased to 14 days in RLS patients with moderate and severe renal impairment (creatinine clearance 20 to 60 mL/min) [ see Clinical Pharmacology (12.3) ].

Discontinuation of Treatment
In clinical trials of patients being treated for RLS with doses up to 0.75 mg once daily, pramipexole dihydrochloride tablets were discontinued without a taper. In a 26 week placebo-controlled clinical trial, patients reported a worsening of RLS symptom severity as compared to their untreated baseline when pramipexole dihydrochloride tablets treatment was suddenly withdrawn [ see Warnings and Precautions (5.10) ].

3 DOSAGE FORMS AND STRENGTHS

0.125 mg: white to off-white, round, flat, beveled edge uncoated tablets, debossed with ‘SG’ on one side ‘126’ on other side. Each tablet contains 0.125 mg pramipexole dihydrochloride monohydrate equivalent to 0.118 mg pramipexole dihydrochloride.

0.25 mg: white to off white, oval, flat, beveled edge uncoated functional scored tablets debossed on one side with ‘S’ on the left side of bisect and ‘G’ on the right side of bisect and other side ‘1’ on the left side and ‘27’ on the right side of the bisect. Each tablet contains 0.25 mg pramipexole dihydrochloride monohydrate equivalent to 0.235 mg pramipexole dihydrochloride.

0.5 mg: white to off white, oval, flat, beveled edge uncoated functional scored tablets debossed on one side with ‘S’ on the left side of bisect and ‘G’ on the right side of bisect and other side ‘1’ on the left side and ‘28’ on the right side of the bisect. Each tablet contains 0.5 mg pramipexole dihydrochloride monohydrate equivalent to 0.47 mg pramipexole dihydrochloride.

0.75 mg: white to off white, oval, flat, beveled edge uncoated tablets, debossed with ‘SG’ on one side ‘129’ on other side. Each tablet contains 0.75 mg pramipexole dihydrochloride monohydrate equivalent to 0.705 mg pramipexole dihydrochloride.

1.0 mg: white to off white, oval, flat, beveled edge uncoated functional scored tablets debossed on one side with ‘S’ on the left side of bisect and ‘G’ on the right side of bisect and other side ‘1’ on the left side and ‘30’ on the right side of the bisect. Each tablet contains 1 mg pramipexole dihydrochloride monohydrate equivalent to 0.94 mg pramipexole dihydrochloride.

1.5 mg: white to off white, oval, flat, beveled edge uncoated functional scored tablets debossed on one side with ‘S’ on the left side of bisect and ‘G’ on the right side of bisect and other side ‘1’ on the left side and ‘31’ on the right side of the bisect. Each tablet contains 1.5 mg pramipexole dihydrochloride monohydrate equivalent to 1.41 mg pramipexole dihydrochloride.

4 CONTRAINDICATIONS

None.

5 WARNINGS AND PRECAUTIONS

5.1 Falling Asleep During Activities of Daily Living and Somnolence

Patients treated with pramipexole have reported falling asleep while engaged in activities of daily living, including the operation of motor vehicles which sometimes resulted in accidents. Although many of these patients reported somnolence while on pramipexole tablets, some perceived that they had no warning signs (sleep attack) such as excessive drowsiness, and believed that they were alert immediately prior to the event. Some of these events had been reported as late as one year after the initiation of treatment.

Somnolence is a common occurrence in patients receiving pramipexole at doses above 1.5 mg/day (0.5 mg three times a day) for Parkinson’s disease. In controlled clinical trials in RLS, patients treated with pramipexole dihydrochloride tablets at doses of 0.25 to 0.75 mg once a day, the incidence of somnolence was 6% compared to an incidence of 3% for placebo-treated patients [ see Adverse Reactions (6.1) ]. It has been reported that falling asleep while engaged in activities of daily living usually occurs in a setting of preexisting somnolence, although patients may not give such a history. For this reason, prescribers should reassess patients for drowsiness or sleepiness, especially since some of the events occur well after the start of treatment. Prescribers should also be aware that patients may not acknowledge drowsiness or sleepiness until directly questioned about drowsiness or sleepiness during specific activities.

Before initiating treatment with pramipexole dihydrochloride tablets, advise patients of the potential to develop drowsiness and specifically ask about factors that may increase the risk for somnolence with pramipexole dihydrochloride tablets such as the use of concomitant sedating medications or alcohol, the presence of sleep disorders, and concomitant medications that increase pramipexole plasma levels (e.g., cimetidine) [ see Clinical Pharmacology (12.3) ]. If a patient develops significant daytime sleepiness or episodes of falling asleep during activities that require active participation (e.g., conversations, eating, etc.), pramipexole dihydrochloride tablets should ordinarily be discontinued. If a decision is made to continue pramipexole dihydrochloride tablets, advise patients not to drive and to avoid other potentially dangerous activities that might result in harm if the patients become somnolent. While dose reduction reduces the degree of somnolence, there is insufficient information to establish that dose reduction will eliminate episodes of falling asleep while engaged in activities of daily living.

5.2 Symptomatic Orthostatic Hypotension

Dopamine agonists, in clinical studies and clinical experience, appear to impair the systemic regulation of blood pressure, with resulting orthostatic hypotension, especially during dose escalation. Parkinson’s disease patients, in addition, appear to have an impaired capacity to respond to an orthostatic challenge. For these reasons, both Parkinson’s disease patients and RLS patients being treated with dopaminergic agonists ordinarily require careful monitoring for signs and symptoms of orthostatic hypotension, especially during dose escalation, and should be informed of this risk.

In clinical trials of pramipexole, however, and despite clear orthostatic effects in normal volunteers, the reported incidence of clinically significant orthostatic hypotension was not greater among those assigned to pramipexole tablets than among those assigned to placebo. This result, especially with the higher doses used in Parkinson’s disease, is clearly unexpected in light of the previous experience with the risks of dopamine agonist therapy.

While this finding could reflect a unique property of pramipexole, it might also be explained by the conditions of the study and the nature of the population enrolled in the clinical trials. Patients were very carefully titrated, and patients with active cardiovascular disease or significant orthostatic hypotension at baseline were excluded. Also, clinical trials in patients with RLS did not incorporate orthostatic challenges with intensive blood pressure monitoring done in close temporal proximity to dosing.

5.3 Impulse Control/Compulsive Behaviors

Case reports and the results of a cross-sectional study suggest that patients can experience intense urges to gamble, increased sexual urges, intense urges to spend money uncontrollably, binge eating, and/or other intense urges and the inability to control these urges while taking one or more of the medications, including pramipexole dihydrochloride tablets, that increase central dopaminergic tone. In some cases, although not all, these urges were reported to have stopped when the dose was reduced or the medication was discontinued. Because patients may not recognize these behaviors as abnormal, it is important for prescribers to specifically ask patients or their caregivers about the development of new or increased gambling urges, sexual urges, uncontrolled spending or other urges while being treated with pramipexole dihydrochloride tablets for Parkinson’s disease or RLS. Physicians should consider dose reduction or stopping the medication if a patient develops such urges while taking pramipexole dihydrochloride tablets.

5.4 Hallucinations and Psychotic-like Behavior

In the three double-blind, placebo-controlled trials in early Parkinson’s disease, hallucinations were observed in 9% (35 of 388) of patients receiving pramipexole dihydrochloride tablets, compared with 2.6% (6 of 235) of patients receiving placebo. In the four double-blind, placebo-controlled trials in advanced Parkinson’s disease, where patients received pramipexole dihydrochloride tablets and concomitant levodopa, hallucinations were observed in 16.5% (43 of 260) of patients receiving pramipexole dihydrochloride tablets compared with 3.8% (10 of 264) of patients receiving placebo. Hallucinations were of sufficient severity to cause discontinuation of treatment in 3.1% of the early Parkinson’s disease patients and 2.7% of the advanced Parkinson's disease patients compared with about 0.4% of placebo patients in both populations.In the three double-blind, placebo-controlled trials in early Parkinson’s disease, hallucinations were observed in 9% (35 of 388) of patients receiving pramipexole dihydrochloride tablets, compared with 2.6% (6 of 235) of patients receiving placebo. In the four double-blind, placebo-controlled trials in advanced Parkinson’s disease, where patients received pramipexole dihydrochloride tablets and concomitant levodopa, hallucinations were observed in 16.5% (43 of 260) of patients receiving pramipexole dihydrochloride tablets compared with 3.8% (10 of 264) of patients receiving placebo. Hallucinations were of sufficient severity to cause discontinuation of treatment in 3.1% of the early Parkinson’s disease patients and 2.7% of the advanced Parkinson's disease patients compared with about 0.4% of placebo patients in both populations.

Age appears to increase the risk of hallucinations attributable to pramipexole. In the early Parkinson’s disease patients, the risk of hallucinations was 1.9 times greater than placebo in patients younger than 65 years and 6.8 times greater than placebo in patients older than 65 years. In the advanced Parkinson's disease patients, the risk of hallucinations was 3.5 times greater than placebo in patients younger than 65 years and 5.2 times greater than placebo in patients older than 65 years.Age appears to increase the risk of hallucinations attributable to pramipexole. In the early Parkinson’s disease patients, the risk of hallucinations was 1.9 times greater than placebo in patients younger than 65 years and 6.8 times greater than placebo in patients older than 65 years. In the advanced Parkinson's disease patients, the risk of hallucinations was 3.5 times greater than placebo in patients younger than 65 years and 5.2 times greater than placebo in patients older than 65 years.

Postmarketing reports with medications used to treat Parkinson’s disease or RLS, including pramipexole, indicate that patients may experience new or worsening mental status and behavioral changes, which may be severe, including psychotic-like behavior during treatment with pramipexole or after starting or increasing the dose of pramipexole. Other drugs prescribed to improve the symptoms of Parkinson’s disease or RLS can have similar effects on thinking and behavior. This abnormal thinking and behavior can consist of one or more of a variety of manifestations including paranoid ideation, delusions, hallucinations, confusion, psychotic-like behavior, symptoms of mania (e.g., insomnia, psychomotor agitation), disorientation, aggressive behavior, agitation, and delirium.

Patients with a major psychotic disorder should ordinarily not be treated with dopamine agonists, including pramipexole, because of the risk of exacerbating the psychosis. In addition, certain medications used to treat psychosis may exacerbate the symptoms of Parkinson’s disease and may decrease the effectiveness of pramipexole [ ]. Patients with a major psychotic disorder should ordinarily not be treated with dopamine agonists, including pramipexole, because of the risk of exacerbating the psychosis. In addition, certain medications used to treat psychosis may exacerbate the symptoms of Parkinson’s disease and may decrease the effectiveness of pramipexole [ see Drug Interactions (7.1) ].

In the RLS clinical trials, one pramipexole-treated patient (of 889) reported hallucinations; this patient discontinued treatment and the symptoms resolved. In the RLS clinical trials, one pramipexole-treated patient (of 889) reported hallucinations; this patient discontinued treatment and the symptoms resolved.

5.5 Dyskinesia

Pramipexole dihydrochloride tablets may cause or exacerbate preexisting dyskinesia.

5.6 Postural Deformity

Postural deformities, including antecollis, camptocormia (Bent Spine Syndrome), and pleurothotonus (Pisa Syndrome), have been reported in patients after starting or increasing the dose of pramipexole. Postural deformity may occur several months after starting treatment or increasing the dose. Reducing the dose or discontinuing pramipexole has been reported to improve postural deformity in some patients, and should be considered if postural deformity occurs.

5.7 Renal Impairment

Since pramipexole is eliminated through the kidneys, caution should be exercised when prescribing pramipexole dihydrochloride tablets to patients with renal impairment [ see Dosage and Administration (2.3), Use in Specific Populations (8.6), and Clinical Pharmacology (12.3)].

5.8 Rhabdomyolysis

A single case of rhabdomyolysis occurred in a 49-year-old male with advanced Parkinson’s disease treated with pramipexole dihydrochloride tablets. The patient was hospitalized with an elevated CPK (10,631 IU/L). The symptoms resolved with discontinuation of the medication.

Advise patients to contact a physician if they experience any unexplained muscle pain, tenderness, or weakness, as these may be symptoms of rhabdomyolysis.

5.9 Retinal Pathology

Human Data
A two-year open-label, randomized, parallel-group safety study of retinal deterioration and vision compared pramipexole dihydrochloride tablets and immediate-release ropinirole. Two hundred thirty four Parkinson’s disease patients (115 on pramipexole, mean dose 3.0 mg/day and 119 on ropinirole, mean dose 9.5 mg/day) were evaluated using a panel of clinical ophthalmological assessments. Of 234 patients who were evaluable, 196 had been treated for two years and 29 were judged to have developed clinical abnormalities that were considered meaningful (19 patients in each treatment arm had received treatment for less than two years). There was no statistical difference in retinal deterioration between the treatment arms; however, the study was only capable of detecting a very large difference between treatments. In addition, because the study did not include an untreated comparison group (placebo treated), it is unknown whether the findings reported in patients treated with either drug are greater than the background rate in an aging population.

Animal Data
Pathologic changes (degeneration and loss of photoreceptor cells) were observed in the retina of albino rats in the 2-year carcinogenicity study. While retinal degeneration was not diagnosed in pigmented rats treated for 2 years, a thinning in the outer nuclear layer of the retina was slightly greater in rats given drug compared with controls. Evaluation of the retinas of albino mice, monkeys, and minipigs did not reveal similar changes. The potential significance of this effect in humans has not been established, but cannot be disregarded because disruption of a mechanism that is universally present in vertebrates (i.e., disk shedding) may be involved [ see Nonclinical Toxicology (13.2) ].

5.10 Events Reported with Dopaminergic Therapy

Although the events enumerated below may not have been reported in association with the use of pramipexole in its development program, they are associated with the use of other dopaminergic drugs. The expected incidence of these events, however, is so low that even if pramipexole caused these events at rates similar to those attributable to other dopaminergic therapies, it would be unlikely that even a single case would have occurred in a cohort of the size exposed to pramipexole in studies to date.

Hyperpyrexia and Confusion
Although not reported with pramipexole in the clinical development program, a symptom complex resembling the neuroleptic malignant syndrome (characterized by elevated temperature, muscular rigidity, altered consciousness, and autonomic instability), with no other obvious etiology, has been reported in association with rapid dose reduction, withdrawal of, or changes in dopaminergic therapy. If possible, avoid sudden discontinuation or rapid dose reduction in patients taking pramipexole dihydrochloride tablets. If the decision is made to discontinue pramipexole dihydrochloride tablets, the dose should be tapered to reduce the risk of hyperpyrexia and confusion [ see Dosage and Administration (2.2) ].

Fibrotic Complications
Cases of retroperitoneal fibrosis, pulmonary infiltrates, pleural effusion, pleural thickening, pericarditis, and cardiac valvulopathy have been reported in patients treated with ergot-derived dopaminergic agents. While these complications may resolve when the drug is discontinued, complete resolution does not always occur.

Although these adverse events are believed to be related to the ergoline structure of these compounds, whether other, nonergot-derived dopamine agonists can cause them is unknown.

Cases of possible fibrotic complications, including peritoneal fibrosis, pleural fibrosis, and pulmonary fibrosis have been reported in the postmarketing experience with pramipexole dihydrochloride tablets. While the evidence is not sufficient to establish a causal relationship between pramipexole dihydrochloride tablets and these fibrotic complications, a contribution of pramipexole dihydrochloride tablets cannot be completely ruled out.

Rebound and Augmentation in RLS
Reports in the literature indicate treatment of RLS with dopaminergic medications can result in rebound: a worsening of symptoms following treatment cessation with greater intensity than described before starting treatment. In a 26 week placebo-controlled clinical trial in patients with RLS, a worsening of symptoms scores (IRLS) beyond their untreated baseline levels was reported more frequently by patients suddenly withdrawn from pramipexole dihydrochloride tablets (up to 0.75 mg once daily) compared to the group assigned to placebo (10% vs. 2%, respectively). The worsening of RLS symptoms was considered generally mild.

Augmentation has also been described during therapy for RLS. Augmentation refers to the earlier onset of symptoms in the evening (or even the afternoon), increase in symptoms, and spread of symptoms to involve other extremities. In a 26 week placebo-controlled clinical trial in patients with RLS, augmentation was reported with greater frequency by patients treated with pramipexole dihydrochloride tablets (up to 0.75 mg once daily) compared to patients who received placebo (12% vs. 9%, respectively). The incidence of augmentation increased with increasing duration of exposure to pramipexole dihydrochloride tablets and to placebo.

The frequency and severity of augmentation and/or rebound after longer-term use of pramipexole dihydrochloride tablets and the appropriate management of these events have not been adequately evaluated in controlled clinical trials.

5.11 Withdrawal Symptoms

Symptoms including apathy, anxiety, depression, fatigue, insomnia, sweating, and pain have been reported during taper or after discontinuation of dopamine agonists, including pramipexole dihydrochloride tablets. These symptoms generally do not respond to levodopa.

Prior to discontinuation of pramipexole dihydrochloride tablets, patients should be informed about potential withdrawal symptoms, and monitored during and after discontinuation. In case of severe withdrawal symptoms, a trial re-administration of a dopamine agonist at the lowest effective dose may be considered.

6 ADVERSE REACTIONS

The following adverse reactions are discussed in greater detail in other sections of the labeling:

- Falling Asleep During Activities of Daily Living and Somnolence [ see Warnings and Precautions (5.1) ].
- Symptomatic Orthostatic Hypotension [ see Warnings and Precautions (5.2) ].
- Impulse Control/Compulsive Behaviors [ see Warnings and Precautions (5.3) ].
- Hallucinations and Psychotic-like Behavior [ see Warnings and Precautions (5.4) ].
- Dyskinesia [ see Warnings and Precautions (5.5) ].
- Postural Deformity [ see Warnings and Precautions (5.6) ].
- Rhabdomyolysis [ see Warnings and Precautions (5.8) ].
- Retinal Pathology [ see Warnings and Precautions (5.9) ].
- Events Reported with Dopaminergic Therapy [ see Warnings and Precautions (5.10) ].
- Withdrawal Symptoms [ see Warnings and Precautions (5.11) ]

6.1 Clinical Trials Experience

Because clinical trials are conducted under widely varying conditions, adverse reaction rates observed in the clinical trials of a drug cannot be directly compared to rates in the clinical trials of another drug and may not reflect the rates observed in clinical practice.

Parkinson's Disease
During the premarketing development of pramipexole, patients with either early or advanced Parkinson’s disease were enrolled in clinical trials. Apart from the severity and duration of their disease, the two populations differed in their use of concomitant levodopa therapy. Patients with early disease did not receive concomitant levodopa therapy during treatment with pramipexole; those with advanced Parkinson's disease all received concomitant levodopa treatment. Because these two populations may have differential risks for various adverse reactions, this section will, in general, present adverse-reaction data for these two populations separately.

Because the controlled trials performed during premarketing development all used a titration design, with a resultant confounding of time and dose, it was impossible to adequately evaluate the effects of dose on the incidence of adverse reactions.

Early Parkinson’s Disease
In the three double-blind, placebo-controlled trials of patients with early Parkinson’s disease, the most common adverse reactions (>5%) that were numerically more frequent in the group treated with pramipexole dihydrochloride tablets were nausea, dizziness, somnolence, insomnia, constipation, asthenia, and hallucinations.

Approximately 12% of 388 patients with early Parkinson’s disease and treated with pramipexole dihydrochloride tablets who participated in the double-blind, placebo-controlled trials discontinued treatment due to adverse reactions compared with 11% of 235 patients who received placebo. The adverse reactions most commonly causing discontinuation of treatment were related to the nervous system (hallucinations [3.1% on pramipexole dihydrochloride tablets vs 0.4% on placebo]; dizziness [2.1% on pramipexole dihydrochloride tablets vs 1% on placebo]; somnolence [1.6% on pramipexole dihydrochloride tablets vs 0% on placebo]; headache and confusion [1.3% and 1.0%, respectively, on pramipexole dihydrochloride tablets vs 0% on placebo]) and gastrointestinal system (nausea [2.1% on pramipexole dihydrochloride tablets vs 0.4% on placebo]).

Adverse-reaction Incidence in Controlled Clinical Studies in Early Parkinson’s Disease:Table 4 lists adverse reactions that occurred in the double-blind, placebo-controlled studies in early Parkinson’s disease that were reported by ≥1% of patients treated with pramipexole dihydrochloride tablets and were numerically more frequent than in the placebo group. In these studies, patients did not receive concomitant levodopa.

Table 4: Adverse-Reactions in Pooled Double-Blind, Placebo-Controlled Trials with Pramipexole Dihydrochloride Tablets in Early Parkinson’s Disease
Body System/Adverse Reaction | Pramipexole dihydrochloride tablets; (N=388); % | Placebo; (N=235); %
Nervous System
Dizziness | 25 | 24
Somnolence | 22 | 9
Insomnia | 17 | 12
Hallucinations | 9 | 3
Confusion | 4 | 1
Amnesia | 4 | 2
Hypesthesia | 3 | 1
Dystonia | 2 | 1
Akathisia | 2 | 0
Thinking abnormalities | 2 | 0
Decreased libido | 1 | 0
Myoclonus | 1 | 0
Digestive System
Nausea | 28 | 18
Constipation | 14 | 6
Anorexia | 4 | 2
Dysphagia | 2 | 0
Body as a Whole
Asthenia | 14 | 12
General edema | 5 | 3
Malaise | 2 | 1
Reaction unevaluable | 2 | 1
Fever | 1 | 0
Metabolic & Nutritional System
Peripheral edema | 5 | 4
Decreased weight | 2 | 0
Special Senses
Vision abnormalities | 3 | 0
Urogenital System
Impotence | 2 | 1

In a fixed-dose study in early Parkinson’s disease, occurrence of the following reactions increased in frequency as the dose increased over the range from 1.5 mg/day to 6 mg/day: postural hypotension, nausea, constipation, somnolence, and amnesia. The frequency of these reactions was generally 2-fold greater than placebo for pramipexole doses greater than 3 mg/day. The incidence of somnolence with pramipexole at a dose of 1.5 mg/day was comparable to that reported for placebo.

Advanced Parkinson’s Disease
In the four double-blind, placebo-controlled trials of patients with advanced Parkinson’s disease, the most common adverse reactions (>5%) that were numerically more frequent in the group treated with pramipexole dihydrochloride tablets and concomitant levodopa were postural (orthostatic) hypotension, dyskinesia, extrapyramidal syndrome, insomnia, dizziness, hallucinations, accidental injury, dream abnormalities, confusion, constipation, asthenia, somnolence, dystonia, gait abnormality, hypertonia, dry mouth, amnesia, and urinary frequency.

Approximately 12% of 260 patients with advanced Parkinson’s disease who received pramipexole dihydrochloride tablets and concomitant levodopa in the double-blind, placebo-controlled trials discontinued treatment due to adverse reactions compared with 16% of 264 patients who received placebo and concomitant levodopa. The reactions most commonly causing discontinuation of treatment were related to the nervous system (hallucinations [2.7% on pramipexole dihydrochloride tablets vs 0.4% on placebo]; dyskinesia [1.9% on pramipexole dihydrochloride tablets vs 0.8% on placebo]) and cardiovascular system (postural [orthostatic] hypotension [2.3% on pramipexole dihydrochloride tablets vs 1.1% on placebo]).

Adverse-reaction Incidence in Controlled Clinical Studies in Advanced Parkinson's Disease:Table 5 lists adverse reactions that occurred in the double-blind, placebo-controlled studies in advanced Parkinson’s disease that were reported by ≥1% of patients treated with pramipexole dihydrochloride tablets and were numerically more frequent than in the placebo group. In these studies, pramipexole dihydrochloride tablets or placebo was administered to patients who were also receiving concomitant levodopa.

Table 5: Adverse-Reactions in Pooled Double-Blind, Placebo-Controlled Trials with Pramipexole Dihydrochloride Tablets in Advanced Parkinson’s Disease
Body System/Adverse Reaction | Pramipexole dihydrochloride tablets (N=260) % | Placebo (N=264) %
Nervous System
Dyskinesia | 47 | 31
Extrapyramidal syndrome | 28 | 26
Insomnia | 27 | 22
Dizziness | 26 | 25
Hallucinations | 17 | 4
Dream abnormalities | 11 | 10
Confusion | 10 | 7
Somnolence | 9 | 6
Dystonia | 8 | 7
Gait abnormalities | 7 | 5
Hypertonia | 7 | 6
Amnesia | 6 | 4
Akathisia | 3 | 2
Thinking abnormalities | 3 | 2
Paranoid reaction | 2 | 0
Delusions | 1 | 0
Sleep disorders | 1 | 0
Cardiovascular System
Postural hypotension | 53 | 48
Body as a Whole
Accidental injury | 17 | 15
Asthenia | 10 | 8
General edema | 4 | 3
Chest pain | 3 | 2
Malaise | 3 | 2
Digestive System
Constipation | 10 | 9
Dry mouth | 7 | 3
Urogenital System
Urinary frequency | 6 | 3
Urinary tract infection | 4 | 3
Urinary incontinence | 2 | 1
Respiratory System
Dyspnea | 4 | 3
Rhinitis | 3 | 1
Pneumonia | 2 | 0
Special Senses
Accommodation abnormalities | 4 | 2
Vision abnormalities | 3 | 1
Diplopia | 1 | 0
Musculoskeletal System
Arthritis | 3 | 1
Twitching | 2 | 0
Bursitis | 2 | 0
Myasthenia | 1 | 0
Metabolic & Nutritional System
Peripheral edema | 2 | 1
Increased creatine PK | 1 | 0
Skin & Appendages
Skin disorders | 2 | 1

Restless Legs Syndrome
Pramipexole dihydrochloride tablets for treatment of RLS have been evaluated for safety in 889 patients, including 427 treated for over six months and 75 for over one year.

The overall safety assessment focuses on the results of three double-blind, placebo-controlled trials, in which 575 patients with RLS were treated with pramipexole dihydrochloride tablets for up to 12 weeks. The most common adverse reactions with pramipexole dihydrochloride tablets in the treatment of RLS (observed in >5% of pramipexole-treated patients and at a rate at least twice that observed in placebo-treated patients) were nausea and somnolence. Occurrences of nausea and somnolence in clinical trials were generally mild and transient.

Approximately 7% of 575 patients treated with pramipexole dihydrochloride tablets during the double-blind periods of three placebo-controlled trials discontinued treatment due to adverse reactions compared to 5% of 223 patients who received placebo. The adverse reaction most commonly causing discontinuation of treatment was nausea (1%).

Table 6 lists reactions that occurred in three double-blind, placebo-controlled studies in RLS patients that were reported by ≥2% of patients treated with pramipexole dihydrochloride tablets and were numerically more frequent than in the placebo group.

Table 6 Adverse-Reactions in Pooled Double-Blind, Placebo-Controlled Trials with Pramipexole dihydrochloride tablets in Restless Legs Syndrome
Body System/Adverse Reaction | Pramipexole dihydrochloride tablets 0.125 - 0.75 mg/day tablets; (N=575); % | Placebo; (N=223); %
Gastrointestinal disorders
Nausea | 16 | 5
Constipation | 4 | 1
Diarrhea | 3 | 1
Dry mouth | 3 | 1
Nervous system disorders
Headache | 16 | 15
Somnolence | 6 | 3
General disorders and administration site conditions
Fatigue | 9 | 7
Infections and infestations
Influenza | 3 | 1

Table 7 summarizes data for adverse reactions that appeared to be dose related in the 12-week fixed dose study.

Table 7 Dose-RelatedAdverse Reactions in a 12-Week Double-Blind, Placebo-Controlled Fixed Dose Study in Restless Legs Syndrome (Occurring in ≥5% of all Patients in the Treatment Phase)

Body System/Adverse Reaction | Pramipexole dihydrochloride tablets 0.25 mg (N=88) % | Pramipexole dihydrochloride tablets 0.5 mg (N=80) % | Pramipexole dihydrochloride tablets 0.75 mg (N=90) % | Placebo (N=86) %
Gastrointestinal disorders
Nausea | 11 | 19 | 27 | 5
Diarrhea | 3 | 1 | 7 | 0
Dyspepsia | 3 | 1 | 4 | 7
Psychiatric disorders
Insomnia | 9 | 9 | 13 | 9
Abnormal dreams | 2 | 1 | 8 | 2
General disorders and administration site conditions
Fatigue | 3 | 5 | 7 | 5
Musculoskeletal and connective tissue disorders
Pain in extremity | 3 | 3 | 7 | 1
Infections and infestations
Influenza | 1 | 4 | 7 | 1
Respiratory, thoracic and mediastinal disorders
Nasal congestion | 0 | 3 | 6 | 1

Adverse Reactions: Relationship to Age, Gender, and Race
Among the adverse reactions in patients treated with pramipexole dihydrochloride tablets, hallucination appeared to exhibit a positive relationship to age in patients with Parkinson’s disease. Although no gender-related differences were observed in Parkinson’s disease patients, nausea and fatigue, both generally transient, were more frequently reported by female than male RLS patients. Less than 4% of patients enrolled were non-Caucasian: therefore, an evaluation of adverse reactions related to race is not possible.

Laboratory Tests
During the development of pramipexole dihydrochloride tablets, no systematic abnormalities on routine laboratory testing were noted.

6.2 Postmarketing Experience

In addition to the adverse events reported during clinical trials, the following adverse reactions have been identified during post-approval use of pramipexole dihydrochloride tablets, primarily in Parkinson’s disease patients. Because these reactions are reported voluntarily from a population of uncertain size, it is not always possible to reliably estimate their frequency or establish a causal relationship to drug exposure. Decisions to include these reactions in labeling are typically based on one or more of the following factors: (1) seriousness of the reaction, (2) frequency of reporting, or (3) strength of causal connection to pramipexole tablets.

Cardiac Disorders:cardiac failure

Gastrointestinal Disorders:vomiting

General Disorders and Administration Site Conditions:withdrawal symptoms [ see Warnings and Precautions (5.11) ]

Metabolism and Nutrition Disorders:syndrome of inappropriate antidiuretic hormone secretion (SIADH), weight increase

Musculoskeletal and Connective Tissue Disorders:postural deformity [ see Warnings and Precautions (5.6) ]

Nervous System Disorders:syncope

Reproductive System and Breast Disorders:priapism

Skin and Subcutaneous Tissue Disorders:skin reactions (including erythema, rash, pruritus, urticaria)

7 DRUG INTERACTIONS

7.1 Dopamine Antagonists

Since pramipexole is a dopamine agonist, it is possible that dopamine antagonists, such as the neuroleptics (phenothiazines, butyrophenones, thioxanthenes) or metoclopramide, may diminish the effectiveness of pramipexole dihydrochloride tablets.

8 USE IN SPECIFIC POPULATIONS

8.1 Pregnancy

Risk Summary
There are no adequate data on the developmental risk associated with the use of pramipexole in pregnant women. No adverse developmental effects were observed in animal studies in which pramipexole was administered to rabbits during pregnancy. Effects on embryofetal development could not be adequately assessed in pregnant rats; however, postnatal growth was inhibited at clinically relevant exposures [see Data].

In the U.S. general population, the estimated background risk of major birth defects and of miscarriage in clinically recognized pregnancies is 2% to 4% and 15% to 20%, respectively. The background risk of major birth defects and miscarriage for the indicated population is unknown.

Data
Animal Data
Oral administration of pramipexole (0.1, 0.5, or 1.5 mg/kg/day) to pregnant rats during the period of organogenesis resulted in a high incidence of total resorption of embryos at the highest dose tested. This increase in embryolethality is thought to result from the prolactin-lowering effect of pramipexole; prolactin is necessary for implantation and maintenance of early pregnancy in rats but not in rabbits or humans. Because of pregnancy disruption and early embryonic loss in this study, the teratogenic potential of pramipexole could not be adequately assessed in rats. The highest no-effect dose for embryolethality in rats was associated with maternal plasma drug exposures (AUC) approximately equal to those in humans receiving the maximum recommended human dose (MRHD) of 4.5 mg/day. There were no adverse effects on embryo-fetal development following oral administration of pramipexole (0.1, 1, or 10 mg/kg/day) to pregnant rabbits during organogenesis (plasma AUC up to approximately 70 times that in humans at the MRHD). Postnatal growth was inhibited in the offspring of rats treated with pramipexole (0.1, 0.5, or 1.5 mg/kg/day) during the latter part of pregnancy and throughout lactation. The no-effect dose for adverse effects on offspring growth (0.1 mg/kg/day) was associated with maternal plasma drug exposures lower than that in humans at the MRHD.

8.2 Lactation

Risk Summary
There are no data on the presence of pramipexole in human milk, the effects of pramipexole on the breastfed infant, or the effects of pramipexole on milk production. However, inhibition of lactation is expected because pramipexole inhibits secretion of prolactin in humans. Pramipexole or metabolites, or both, are present in rat milk [see Data].

The developmental and health benefits of breastfeeding should be considered along with the mother’s clinical need for pramipexole and any potential adverse effects on the breastfed infant from pramipexole or from the underlying maternal condition.

Data
In a study of radio-labeled pramipexole, pramipexole or metabolites, or both, were present in rat milk at concentrations three to six times higher than those in maternal plasma.

8.4 Pediatric Use

Safety and effectiveness of pramipexole dihydrochloride tablets in pediatric patients has not been established.

8.5 Geriatric Use

Pramipexole total oral clearance is approximately 30% lower in subjects older than 65 years compared with younger subjects, because of a decline in pramipexole renal clearance due to an age-related reduction in renal function. This resulted in an increase in elimination half-life from approximately 8.5 hours to 12 hours.

In clinical studies with Parkinson’s disease patients, 38.7% of patients were older than 65 years. There were no apparent differences in efficacy or safety between older and younger patients, except that the relative risk of hallucination associated with the use of pramipexole dihydrochloride tablets was increased in the elderly.

In clinical studies with RLS patients, 22% of patients were at least 65 years old. There were no apparent differences in efficacy or safety between older and younger patients.

8.6 Renal Impairment

The elimination of pramipexole is dependent on renal function. Pramipexole clearance is extremely low in dialysis patients, as a negligible amount of pramipexole is removed by dialysis. Caution should be exercised when administering pramipexole dihydrochloride tablets to patients with renal disease [see Dosage and Administration (2.2), Warnings and Precautions (5.7) , and Clinical Pharmacology (12.3) ].

10 OVERDOSAGE

There is no clinical experience with significant overdosage. One patient took 11 mg/day of pramipexole for 2 days in a clinical trial for an investigational use. Blood pressure remained stable although pulse rate increased to between 100 and 120 beats/minute. No other adverse reactions were reported related to the increased dose.

There is no known antidote for overdosage of a dopamine agonist. If signs of central nervous system stimulation are present, a phenothiazine or other butyrophenone neuroleptic agent may be indicated; the efficacy of such drugs in reversing the effects of overdosage has not been assessed. Management of overdose may require general supportive measures along with gastric lavage, intravenous fluids, and electrocardiogram monitoring.

11 DESCRIPTION

Pramipexole dihydrochloride tablets contain pramipexole dihydrochloride (as a monohydrate). Pramipexole is a nonergot dopamine agonist. The chemical name of pramipexole dihydrochloride monohydrate is (S)-2-amino-4,5,6,7-tetrahydro-6-(propylamino)benzothiazole dihydrochloride monohydrate. Its empirical formula is C10H17N3S ·2HCl ·H2O, and its molecular weight is 302.27. The structural formula is:

Pramipexole dihydrochloride is a white to almost white crystalline powder. Melting occurs in the range of 296°C to 301°C, with decomposition. Pramipexole Dihydrochloride is freely soluble in water, soluble in methanol, sparingly soluble to slightly soluble in ethanol (96%) and practically insoluble in methylene chloride.

Pramipexole dihydrochloride tablets 0.125 mg:
Each tablet contains 0.125 mg pramipexole dihydrochloride monohydrate equivalent to 0.118 mg pramipexole dihydrochloride.

Pramipexole dihydrochloride tablets 0.25 mg:
Each tablet contains 0.25 mg pramipexole dihydrochloride monohydrate equivalent to 0.235 mg pramipexole dihydrochloride.

Pramipexole dihydrochloride tablets 0.5 mg:
Each tablet contains 0.5 mg pramipexole dihydrochloride monohydrate equivalent to 0.47 mg pramipexole dihydrochloride.

Pramipexole dihydrochloride tablets 0.75 mg:
Each tablet contains 0.75 mg pramipexole dihydrochloride monohydrate equivalent to 0.705 mg pramipexole dihydrochloride.

Pramipexole dihydrochloride tablets 1 mg:
Each tablet contains 1 mg pramipexole dihydrochloride monohydrate equivalent to 0.94 mg pramipexole dihydrochloride.

Pramipexole dihydrochloride tablets 1.5 mg:
Each tablet contains 1.5 mg pramipexole dihydrochloride monohydrate equivalent to 1.41 mg pramipexole dihydrochloride.

Inactive ingredients for all strengths of pramipexole dihydrochloride tablets consist of mannitol, corn starch, colloidal silicon dioxide, povidone, and magnesium stearate.

12 CLINICAL PHARMACOLOGY

12.1 Mechanism of Action

Pramipexole is a non-ergot dopamine agonist with high relative in vitrospecificity and full intrinsic activity at the D2subfamily of dopamine receptors, binding with higher affinity to D3than to D2or D4receptor subtypes.

Parkinson’s Disease
The precise mechanism of action of pramipexole as a treatment for Parkinson’s disease is unknown, although it is believed to be related to its ability to stimulate dopamine receptors in the striatum. This conclusion is supported by electrophysiologic studies in animals that have demonstrated that pramipexole influences striatal neuronal firing rates via activation of dopamine receptors in the striatum and the substantia nigra, the site of neurons that send projections to the striatum. The relevance of D3receptor binding in Parkinson’s disease is unknown.

Restless Legs Syndrome (RLS)
The precise mechanism of action of pramipexole dihydrochloride tablets as a treatment for RLS is unknown. Although the pathophysiology of RLS is largely unknown, neuropharmacological evidence suggests primary dopaminergic system involvement. Positron Emission Tomographic (PET) studies suggest that a mild striatal presynaptic dopaminergic dysfunction may be involved in the pathogenesis of RLS.

12.2 Pharmacodynamics

The effect of pramipexole on the QT interval of the ECG was investigated in a clinical study in 60 healthy male and female volunteers. All subjects initiated treatment with 0.375 mg extended release pramipexole tablets administered once daily, and were up-titrated every 3 days to 2.25 mg and 4.5 mg daily, a faster rate of titration than recommended in the label. No dose- or exposure-related effect on mean QT intervals was observed; however, the study did not have a valid assessment of assay sensitivity. The effect of pramipexole on QTc intervals at higher exposures achieved either due to drug interactions (e.g., with cimetidine), renal impairment, or at higher doses has not been systematically evaluated.

Although mean values remained within normal reference ranges throughout the study, supine systolic blood pressure (SBP), diastolic blood pressure (DBP), and pulse rate for subjects treated with pramipexole generally increased during the rapid up-titration phase, by 10 mmHg, 7 mmHg, and 10 bpm higher than placebo, respectively. Higher SBP, DBP, and pulse rates compared to placebo were maintained until the pramipexole doses were tapered; values on the last day of tapering were generally similar to baseline values. Such effects have not been observed in clinical studies with Parkinson’s disease patients, who were titrated according to labeled recommendations.

12.3 Pharmacokinetics

Pramipexole displays linear pharmacokinetics over the clinical dosage range. Its terminal half-life is about 8 hours in young healthy volunteers and about 12 hours in elderly volunteers. Steady-state concentrations are achieved within 2 days of dosing.

Absorption
Pramipexole is rapidly absorbed, reaching peak concentrations in approximately 2 hours. The absolute bioavailability of pramipexole is greater than 90%, indicating that it is well absorbed and undergoes little presystemic metabolism. Food does not affect the extent of pramipexole absorption, although the time of maximum plasma concentration (Tmax) is increased by about 1 hour when the drug is taken with a meal.

Distribution
Pramipexole is extensively distributed, having a volume of distribution of about 500 L (coefficient of variation [CV]=20%). It is about 15% bound to plasma proteins. Pramipexole distributes into red blood cells as indicated by an erythrocyte-to-plasma ratio of approximately 2.

Metabolism
Pramipexole is metabolized only to a negligible extent (<10%). No specific active metabolite has been identified in human plasma or urine.

Elimination
Urinary excretion is the major route of pramipexole elimination, with 90% of a pramipexole dose recovered in urine, almost all as unchanged drug. The renal clearance of pramipexole is approximately 400 mL/min (CV=25%), approximately three times higher than the glomerular filtration rate. Thus, pramipexole is secreted by the renal tubules, probably by the organic cation transport system.

Pharmacokinetics in Specific Populations
Because therapy with pramipexole dihydrochloride tablets is initiated at a low dose and gradually titrated upward according to clinical tolerability to obtain the optimum therapeutic effect, adjustment of the initial dose based on gender, weight, race, or age is not necessary. However, renal insufficiency, which can cause a large decrease in the ability to eliminate pramipexole, may necessitate dosage adjustment [see Dosage and Administration (2.2) ].

Gender
Pramipexole clearance is about 30% lower in women than in men, but this difference can be accounted for by differences in body weight. There is no difference in half-life between males and females.

Age
Pramipexole clearance decreases with age as the half-life and clearance are about 40% longer and 30% lower, respectively, in elderly (aged 65 years or older) compared with young healthy volunteers (aged less than 40 years). This difference is most likely due to the reduction in renal function with age, since pramipexole clearance is correlated with renal function, as measured by creatinine clearance.

Race
No racial differences in metabolism and elimination have been identified.

Parkinson’s Disease Patients
A cross-study comparison of data suggests that the clearance of pramipexole may be reduced by about 30% in Parkinson’s disease patients compared with healthy elderly volunteers. The reason for this difference appears to be reduced renal function in Parkinson’s disease patients, which may be related to their poorer general health. The pharmacokinetics of pramipexole were comparable between early and advanced Parkinson’s disease patients.

Restless Legs Syndrome Patients
A cross-study comparison of data suggests that the pharmacokinetic profile of pramipexole administered once daily in RLS patients is similar to the pharmacokinetic profile of pramipexole in healthy volunteers.

Hepatic Impairment
The influence of hepatic insufficiency on pramipexole pharmacokinetics has not been evaluated. Because approximately 90% of the recovered dose is excreted in the urine as unchanged drug, hepatic impairment would not be expected to have a significant effect on pramipexole elimination.

Renal Impairment
Clearance of pramipexole was about 75% lower in patients with severe renal impairment (creatinine clearance approximately 20 mL/min) and about 60% lower in patients with moderate impairment (creatinine clearance approximately 40 mL/min) compared with healthy volunteers [see Warnings and Precautions (5.7) and Dosage and Administration (2.2) ]. In patients with varying degrees of renal impairment, pramipexole clearance correlates well with creatinine clearance. Therefore, creatinine clearance can be used as a predictor of the extent of decrease in pramipexole clearance.

Drug Interactions
Carbidopa/levodopa:Carbidopa/levodopa did not influence the pharmacokinetics of pramipexole in healthy volunteers (N=10). Pramipexole did not alter the extent of absorption (AUC) or the elimination of carbidopa/levodopa, although it caused an increase in levodopa Cmaxby about 40% and a decrease in Tmaxfrom 2.5 to 0.5 hours.

Selegiline:In healthy volunteers (N=11), selegiline did not influence the pharmacokinetics of pramipexole.

Amantadine:Population pharmacokinetic analyses suggest that amantadine may slightly decrease the oral clearance of pramipexole.

Cimetidine:Cimetidine, a known inhibitor of renal tubular secretion of organic bases via the cationic transport system, caused a 50% increase in pramipexole AUC and a 40% increase in half-life (N=12).

Probenecid:Probenecid, a known inhibitor of renal tubular secretion of organic acids via the anionic transporter, did not noticeably influence Pramipexole pharmacokinetics (N=12).

Other drugs eliminated via renal secretion:Population pharmacokinetic analysis suggests that coadministration of drugs that are secreted by the cationic transport system (e.g., cimetidine, ranitidine, diltiazem, triamterene, verapamil, quinidine, and quinine) decreases the oral clearance of pramipexole by about 20%, while those secreted by the anionic transport system (e.g., cephalosporins, penicillins, indomethacin, hydrochlorothiazide, and chlorpropamide) are likely to have little effect on the oral clearance of pramipexole. Other known organic cation transport substrates and/or inhibitors (e.g., cisplatin and procainamide) may also decrease the clearance of pramipexole.

CYP interactions:Inhibitors of cytochrome P450 enzymes would not be expected to affect pramipexole elimination because pramipexole is not appreciably metabolized by these enzymes in vivoor in vitro. Pramipexole does not inhibit CYP enzymes CYP1A2, CYP2C9, CYP2C19, CYP2E1, and CYP3A4. Inhibition of CYP2D6 was observed with an apparent Ki of 30 μM, indicating that pramipexole will not inhibit CYP enzymes at plasma concentrations observed following the clinical dose of 4.5 mg/day (1.5 mg TID).

13 NONCLINICAL TOXICOLOGY

13.1 Carcinogenesis, Mutagenesis, Impairment of Fertility

Two-year carcinogenicity studies with pramipexole have been conducted in mice and rats. Pramipexole was administered in the diet to mice at doses up to 10 mg/kg/day (or approximately 10 times the maximum recommended human dose (MRHD) for Parkinson’s disease of 4.5 mg/day on a mg/m^2basis). Pramipexole was administered in the diet to rats at doses up to 8 mg/kg/day. These doses were associated with plasma AUCs up to approximately 12 times that in humans at the MRHD. No significant increases in tumors occurred in either species.

Pramipexole was not mutagenic or clastogenic in a battery of in vitro (bacterial reverse mutation, V79/HGPRT gene mutation, chromosomal aberration in CHO cells) and in vivo (mouse micronucleus) assays.

In rat fertility studies, pramipexole at a dose of 2.5 mg/kg/day (5 times the MRHD on a mg/m^2basis), prolonged estrus cycles and inhibited implantation. These effects were associated with reductions in serum levels of prolactin, a hormone necessary for implantation and maintenance of early pregnancy in rats.

13.2 Animal Toxicology and/or Pharmacology

Retinal Pathology in Rats
Pathologic changes (degeneration and loss of photoreceptor cells) were observed in the retina of albino rats in the 2-year carcinogenicity study with pramipexole. These findings were first observed during week 76 and were dose-dependent in animals receiving 2 or 8 mg/kg/day (plasma AUCs equal to 2.5 and 12.5 times that in humans at the MRHD). In a similar study of pigmented rats with 2 years exposure to pramipexole at 2 or 8 mg/kg/day, retinal degeneration was not observed. Animals given drug had thinning in the outer nuclear layer of the retina that was only slightly greater (by morphometric analysis) than that seen in control rats.

Investigative studies demonstrated that pramipexole reduced the rate of disk shedding from the photoreceptor rod cells of the retina in albino rats, which was associated with enhanced sensitivity to the damaging effects of light. In a comparative study, degeneration and loss of photoreceptor cells occurred in albino rats after 13 weeks of treatment with 25 mg/kg/day of pramipexole (54 times the MRHD on a mg/m^2basis) and constant light (100 lux) but not in pigmented rats exposed to the same dose and higher light intensities (500 lux). Thus, the retina of albino rats is considered to be uniquely sensitive to the damaging effects of pramipexole and light. Similar changes in the retina did not occur in a 2-year carcinogenicity study in albino mice treated with 0.3, 2, or 10 mg/kg/day (0.3, 2.2 and 11 times the MRHD on a mg/m^2basis). Evaluation of the retinas of monkeys given 0.1, 0.5, or 2.0 mg/kg/day of pramipexole (0.4, 2.2, and 8.6 times the MRHD on a mg/m^2basis) for 12 months and minipigs given 0.3, 1, or 5 mg/kg/day of pramipexole for 13 weeks also detected no changes.

The potential significance of this effect in humans has not been established, but cannot be disregarded because disruption of a mechanism that is universally present in vertebrates (i.e., disk shedding) may be involved.

Fibro-osseous Proliferative Lesions in Mice
An increased incidence of fibro-osseous proliferative lesions occurred in the femurs of female mice treated for 2 years with 0.3, 2.0, or 10 mg/kg/day (0.3, 2.2, and 11 times the MRHD on a mg/m^2basis). Similar lesions were not observed in male mice or rats and monkeys of either sex that were treated chronically with pramipexole. The significance of this lesion to humans is not known.

14 CLINICAL STUDIES

14.1 Parkinson’s Disease

The effectiveness of pramipexole dihydrochloride tablets in the treatment of Parkinson's disease was evaluated in a multinational drug development program consisting of seven randomized, controlled trials. Three were conducted in patients with early Parkinson’s disease who were not receiving concomitant levodopa, and four were conducted in patients with advanced Parkinson’s disease who were receiving concomitant levodopa. Among these seven studies, three studies provide the most persuasive evidence of pramipexole’s effectiveness in the management of patients with Parkinson's disease who were and were not receiving concomitant levodopa. Two of these three trials enrolled patients with early Parkinson’s disease (not receiving levodopa), and one enrolled patients with advanced Parkinson's disease who were receiving maximally tolerated doses of levodopa.

In all studies, the Unified Parkinson’s Disease Rating Scale (UPDRS), or one or more of its subparts, served as the primary outcome assessment measure. The UPDRS is a four-part multi-item rating scale intended to evaluate mentation (part I), Activities of Daily Living (ADL) (part II), motor performance (part III), and complications of therapy (part IV).

Part II of the UPDRS contains 13 questions relating to ADL, which are scored from 0 (normal) to 4 (maximal severity) for a maximum (worst) score of 52. Part III of the UPDRS contains 27 questions (for 14 items) and is scored as described for part II. It is designed to assess the severity of the cardinal motor findings in patients with Parkinson's disease (e.g., tremor, rigidity, bradykinesia, postural instability, etc.), scored for different body regions, and has a maximum (worst) score of 108.

Studies in Patients with Early Parkinson’s Disease
Patients (N=599) in the two studies of early Parkinson’s disease had a mean disease duration of 2 years, limited or no prior exposure to levodopa (generally none in the preceding 6 months), and were not experiencing the “on-off” phenomenon and dyskinesia characteristic of later stages of the disease.

One of the two early Parkinson's disease studies (N=335) was a double-blind, placebo-controlled, parallel trial consisting of a 7-week dose-escalation period and a 6-month maintenance period. Patients could be on selegiline, anticholinergics, or both, but could not be on levodopa products or amantadine. Patients were randomized to pramipexole dihydrochloride tablets or placebo. Patients treated with pramipexole dihydrochloride tablets had a starting daily dose of 0.375 mg and were titrated to a maximally tolerated dose, but no higher than 4.5 mg/day in three divided doses. At the end of the 6-month maintenance period, the mean improvement from baseline on the UPDRS part II (ADL) total score was 1.9 in the group receiving pramipexole dihydrochloride tablets and -0.4 in the placebo group, a difference that was statistically significant. The mean improvement from baseline on the UPDRS part III total score was 5.0 in the group receiving pramipexole dihydrochloride tablets and -0.8 in the placebo group, a difference that was also statistically significant. A statistically significant difference between groups in favor of pramipexole dihydrochloride tablets was seen beginning at week 2 of the UPDRS part II (maximum dose 0.75 mg/day) and at week 3 of the UPDRS part III (maximum dose 1.5 mg/day).

The second early Parkinson’s disease study (N=264) was a double-blind, placebo-controlled, parallel trial consisting of a 6-week dose-escalation period and a 4-week maintenance period. Patients could be on selegiline, anticholinergics, amantadine, or any combination of these, but could not be on levodopa products. Patients were randomized to 1 of 4 fixed doses of pramipexole dihydrochloride tablets (1.5 mg, 3.0 mg, 4.5 mg, or 6.0 mg per day) or placebo. At the end of the 4-week maintenance period, the mean improvement from baseline on the UPDRS part II total score was 1.8 in the patients treated with pramipexole dihydrochloride tablets, regardless of assigned dose group, and 0.3 in placebo-treated patients. The mean improvement from baseline on the UPDRS part III total score was 4.2 in patients treated with pramipexole dihydrochloride tablets and 0.6 in placebo-treated patients. No dose-response relationship was demonstrated. The between-treatment differences on both parts of the UPDRS were statistically significant in favor of pramipexole dihydrochloride tablets for all doses.

No differences in effectiveness based on age or gender were detected. There were too few non-Caucasian patients to evaluate the effect of race. Patients receiving selegiline or anticholinergics had responses similar to patients not receiving these drugs.

Studies in Patients with Advanced Parkinson’s Disease
In the advanced Parkinson's disease study, the primary assessments were the UPDRS and daily diaries that quantified amounts of “on” and “off” time.

Patients in the advanced Parkinson’s disease study (N=360) had a mean disease duration of 9 years, had been exposed to levodopa for long periods of time (mean 8 years), used concomitant levodopa during the trial, and had “on-off” periods.

The advanced Parkinson’s disease study was a double-blind, placebo-controlled, parallel trial consisting of a 7-week dose-escalation period and a 6-month maintenance period. Patients were all treated with concomitant levodopa products and could additionally be on concomitant selegiline, anticholinergics, amantadine, or any combination. Patients treated with pramipexole dihydrochloride tablets had a starting dose of 0.375 mg/day and were titrated to a maximally tolerated dose, but no higher than 4.5 mg/day in three divided doses. At selected times during the 6-month maintenance period, patients were asked to record the amount of “off,” “on,” or “on with dyskinesia” time per day for several sequential days. At the end of the 6-month maintenance period, the mean improvement from baseline on the UPDRS part II total score was 2.7 in the group treated with pramipexole dihydrochloride tablets and 0.5 in the placebo group, a difference that was statistically significant. The mean improvement from baseline on the UPDRS part III total score was 5.6 in the group treated with pramipexole dihydrochloride tablets and 2.8 in the placebo group, a difference that was statistically significant. A statistically significant difference between groups in favor of pramipexole dihydrochloride tablets was seen at week 3 of the UPDRS part II (maximum dose 1.5 mg/day) and at week 2 of the UPDRS part III (maximum dose 0.75 mg/day). Dosage reduction of levodopa was allowed during this study if dyskinesia (or hallucinations) developed; levodopa dosage reduction occurred in 76% of patients treated with pramipexole dihydrochloride tablets versus 54% of placebo patients. On average, the levodopa dose was reduced 27%.

The mean number of “off” hours per day during baseline was 6 hours for both treatment groups. Throughout the trial, patients treated with pramipexole dihydrochloride tablets had a mean of 4 “off” hours per day, while placebo-treated patients continued to experience 6 “off” hours per day.

No differences in effectiveness based on age or gender were detected. There were too few non-Caucasian patients to evaluate the effect of race.

14.2 Restless Legs Syndrome

The efficacy of pramipexole dihydrochloride tablets in the treatment of RLS was evaluated in a multinational drug development program consisting of 4 randomized, double-blind, placebo-controlled trials. This program included approximately 1000 patients with moderate to severe RLS; patients with RLS secondary to other conditions (e.g., pregnancy, renal failure, and anemia) were excluded. All patients were administered pramipexole dihydrochloride tablets (0.125 mg, 0.25 mg, 0.5 mg, or 0.75 mg) or placebo once daily 2 to 3 hours before going to bed. Across the 4 studies, the mean duration of RLS was 4.6 years (range of 0 to 56 years), mean age was approximately 55 years (range of 18 to 81 years), and approximately 66.6% were women.

Key diagnostic criteria for RLS are: an urge to move the legs usually accompanied or caused by uncomfortable and unpleasant leg sensations; symptoms begin or worsen during periods of rest or inactivity such as lying or sitting; symptoms are partially or totally relieved by movement such as walking or stretching at least as long as the activity continues; and symptoms are worse or occur only in the evening or night. Difficulty falling asleep may frequently be associated with symptoms of RLS.

The two outcome measures used to assess the effect of treatment were the International RLS Rating Scale (IRLS Scale) and a Clinical Global Impression -Improvement (CGI-I) assessment. The IRLS Scale contains 10 items designed to assess the severity of sensory and motor symptoms, sleep disturbance, daytime somnolence, and impact on activities of daily living and mood associated with RLS. The range of scores is 0 to 40, with 0 being absence of RLS symptoms and 40 the most severe symptoms. The CGI-I is designed to assess clinical progress (global improvement) on a 7-point scale.

In Study 1, fixed doses of pramipexole dihydrochloride tablets were compared to placebo in a study of 12 weeks duration. A total of 344 patients were randomized equally to the 4 treatment groups. Patients treated with pramipexole dihydrochloride tablets (n=254) had a starting dose of 0.125 mg/day and were titrated to one of the three randomized doses (0.25, 0.5, 0.75 mg/day) in the first three weeks of the study. The mean improvement from baseline on the IRLS Scale total score and the percentage of CGI-I responders for each of the pramipexole dihydrochloride tablets treatment groups compared to placebo are summarized in Table 8. All treatment groups reached statistically significant superiority compared to placebo for both endpoints. There was no clear evidence of a dose-response across the 3 randomized dose groups.

Table 8 Mean Changes from Baseline to Week 12 in IRLS Score and CGI-I (Study 1)

 | Pramipexole dihydrochloride tablets 0.25 mg | Pramipexole dihydrochloride tablets 0.5 mg | Pramipexole dihydrochloride tablets 0.75 mg | Pramipexole dihydrochloride tablets Total | Placebo
No. Patients | 88 | 79 | 87 | 254 | 85
IRLS score | -13.1 | -13.4 | -14.4 | -13.6 | -9.4
CGI-I responders* | 74.7% | 67.9% | 72.9% | 72% | 51.2%

*CGI-I responders = “much improved” and “very much improved”

Study 2 was a randomized-withdrawal study, designed to demonstrate the sustained efficacy of pramipexole for treatment of RLS after a period of six months. RLS patients who responded to pramipexole dihydrochloride tablets treatment in a preceding 6-month open-label treatment phase (defined as having a CGI-I rating of “very much improved” or “much improved” compared to baseline and an IRLS score of 15 or below) were randomized to receive either continued active treatment (n=78) or placebo (n=69) for 12 weeks. The primary endpoint of this study was time to treatment failure, defined as any worsening on the CGI-I score along with an IRLS Scale total score above 15.

In patients who had responded to 6-month open label treatment with pramipexole dihydrochloride tablets, the administration of placebo led to a rapid decline in their overall conditions and return of their RLS symptoms. At the end of the 12-week observation period, 85% of patients treated with placebo had failed treatment, compared to 21% treated with blinded pramipexole, a difference that was highly statistically significant. The majority of treatment failures occurred within 10 days of randomization. For the patients randomized, the distribution of doses was: 7 on 0.125 mg, 44 on 0.25 mg, 47 on 0.5 mg, and 49 on 0.75 mg.

Study 3 was a 6-week study, comparing a flexible dose of pramipexole dihydrochloride tablets to placebo. In this study, 345 patients were randomized in a 2:1 ratio to pramipexole dihydrochloride tablets or placebo. The mean improvement from baseline on the IRLS Scale total score was -12 for pramipexole dihydrochloride tablets-treated patients and -6 for placebo-treated patients. The percentage of CGI-I responders was 63% for pramipexole dihydrochloride tablets-treated patients and 32% for placebo-treated patients. The between-group differences were statistically significant for both outcome measures. For the patients randomized to pramipexole dihydrochloride tablets, the distribution of achieved doses was: 35 on 0.125 mg, 51 on 0.25 mg, 65 on 0.5 mg, and 69 on 0.75 mg.

Study 4 was a 3-week study, comparing 4 fixed doses of pramipexole dihydrochloride tablets, 0.125 mg, 0.25 mg, 0.5 mg, and 0.75 mg, to placebo. Approximately 20 patients were randomized to each of the 5 dose groups. The mean improvement from baseline on the IRLS Scale total score and the percentage of CGI-I responders for each of the pramipexole dihydrochloride tablets treatment groups compared to placebo are summarized in Table 9. In this study, the 0.125 mg dose group was not significantly different from placebo. On average, the 0.5 mg dose group performed better than the 0.25 mg dose group, but there was no difference between the 0.5 mg and 0.75 mg dose groups.

Table 9 Mean Changes from Baseline to Week 13 in IRLS Score and CGI-I (Study 4)

 | Pramipexole dihydrochloride tablets 0.125 mg | Pramipexole dihydrochloride tablets 0.25 mg | Pramipexole dihydrochloride tablets 0.5 mg | Pramipexole dihydrochloride tablets 0.75 mg | Pramipexole dihydrochloride tablets Total | Placebo
No. Patients | 21 | 22 | 22 | 21 | 86 | 21
IRLS score | -11.7 | -15.3 | -17.6 | -15.2 | -15.0 | -6.2
CGI-I responders* | 61.9% | 68.2% | 86.4% | 85.7% | 75.6% | 42.9%

*CGI-I responders = “much improved” and “very much improved”

No differences in effectiveness based on age or gender were detected. There were too few non-Caucasian patients to evaluate the effect of race.

16 HOW SUPPLIED/STORAGE AND HANDLING

16.1 How Supplied

Pramipexole dihydrochloride tablets are available as follows:

0.125 mg, white to off-white, round, flat, beveled edge uncoated tablets, debossed with ‘SG’ on one side ‘126’ on other side.

NDC 60429-085-90, bottle of 90 tablets

0.25 mg, white to off white, oval, flat, beveled edge uncoated functional scored tablets debossed on one side with ‘S’ on the left side of bisect and ‘G’ on the right side of bisect and other side ‘1’ on the left side and ‘27’ on the right side of the bisect.

NDC 60429-086-90, bottle of 90 tablets

0.5 mg, white to off white, oval, flat, beveled edge uncoated functional scored tablets debossed on one side with ‘S’ on the left side of bisect and ‘G’ on the right side of bisect and other side ‘1’ on the left side and ‘28’ on the right side of the bisect.

NDC 60429-087-90, bottle of 90 tablets

0.75 mg, white to off white, oval, flat, beveled edge uncoated tablets, debossed with ‘SG’ on one side ‘129’ on other side.

NDC 60429-088-90, bottle of 90 tablets

1.0 mg, white to off white, oval, flat, beveled edge uncoated functional scored tablets debossed on one side with ‘S’ on the left side of bisect and ‘G’ on the right side of bisect and other side ‘1’ on the left side and ‘30’ on the right side of the bisect.

NDC 60429-089-90, bottle of 90 tablets

1.5 mg, white to off white, oval, flat, beveled edge uncoated functional scored tablets debossed on one side with ‘S’ on the left side of bisect and ‘G’ on the right side of bisect and other side ‘1’ on the left side and ‘31’ on the right side of the bisect.

NDC 60429-090-90, bottle of 90 tablets

16.2 Storage and Handling

Store at 20 ºC to 25ºC (68 ºF to 77ºF); (see USP controlled Room Temperature).
Protect from light.

Store in a safe place out of the reach of children.

17 PATIENT COUNSELING INFORMATION

Advise the patient to read the FDA-approved patient labeling (Patient Information).

Dosing Instructions

Instruct patients to take pramipexole dihydrochloride tablets only as prescribed. If a dose is missed, advise patients not to double their next dose.

Pramipexole dihydrochloride tablets can be taken with or without food. If patients develop nausea, advise that taking pramipexole dihydrochloride tablets with food may reduce the occurrence of nausea.

Pramipexole is the active ingredient that is in both pramipexole dihydrochloride tablets and extended-release pramipexole tablets. Ensure that patients do not take both extended-release pramipexole and pramipexole dihydrochloride tablets.

Sedating Effects

Alert patients to the potential sedating effects associated with pramipexole dihydrochloride tablets, including somnolence and the possibility of falling asleep while engaged in activities of daily living. Since somnolence is a frequent adverse reaction with potentially serious consequences, patients should neither drive a car nor engage in other potentially dangerous activities until they have gained sufficient experience with pramipexole dihydrochloride tablets to gauge whether or not it affects their mental and/or motor performance adversely. Advise patients that if increased somnolence or new episodes of falling asleep during activities of daily living (e.g., conversations or eating) are experienced at any time during treatment, they should not drive or participate in potentially dangerous activities until they have contacted their physician. Because of possible additive effects, advise caution when patients are taking other sedating medications or alcohol in combination with pramipexole dihydrochloride tablets and when taking concomitant medications that increase plasma levels of pramipexole (e.g., cimetidine) [ see Warnings and Precautions (5.1) ].

Postural (Orthostatic) Hypotension

Advise patients that they may develop postural (orthostatic) hypotension, with or without symptoms such as dizziness, nausea, fainting or blackouts, and sometimes, sweating. Hypotension may occur more frequently during initial therapy. Accordingly, caution patients against rising rapidly after sitting or lying down, especially if they have been doing so for prolonged periods and especially at the initiation of treatment with Pramipexole dihydrochloride tablets [ see Warnings and Precautions (5.2) ].

Impulse Control Symptoms Including Compulsive Behaviors

Alert patients and their caregivers to the possibility that they may experience intense urges to spend money uncontrollably, intense urges to gamble, increased sexual urges, binge eating and/or other intense urges and the inability to control these urges while taking pramipexole dihydrochloride tablets [ see Warnings and Precautions (5.3) ].

Hallucinations and Pyschotic-like Behavior

Inform patients that hallucinations and other psychotic-like behavior can occur. In patients with Parkinson’s disease, the elderly are at a higher risk than younger patients [ see Warnings and Precautions (5.4) ].

Withdrawal-Emergent Hyperpyrexia and Confusion

Advise patients who have been prescribed a lower dose or who have been withdrawn from the drug to notify their healthcare provider if they have symptoms such as fever, muscular rigidity, or altered consciousness [ see Warnings and Precautions (5.10) ].

Withdrawal Symptoms

Advise patients that withdrawal symptoms may occur during or after discontinuation or dose reduction of pramipexole dihydrochloride tablets. Advise patients who have been prescribed a lower dose or who have been withdrawn from the drug to notify their healthcare provider if they have withdrawal symptoms such as apathy, anxiety, depression, fatigue, insomnia, sweating, or pain. Notify patients that in case of severe withdrawal symptoms, a trial re-administration of a dopamine agonist at the lowest effective dose may be considered [ see Warnings and Precautions (5.11) ].

Pregnancy

Because the teratogenic potential of pramipexole has not been completely established in laboratory animals, and because experience in humans is limited, advise women to notify their physicians if they become pregnant or intend to become pregnant during therapy [ see Use in Specific Populations (8.1) ].

Lactation

Because of the possibility that pramipexole may be excreted in breast milk, advise women to notify their physicians if they intend to breast-feed or are breast-feeding an infant [ see Use in Specific Populations (8.2) ].

Manufactured by:
ScieGen Pharmaceuticals, Inc.
Hauppauge, NY 11788 USA

Rev. 10/2025

Marketed by:
GSMS, Inc.
Camarillo, CA 93012 USA

PATIENT INFORMATION
PRAMIPEXOLE (pram’’-i-pex’-ole) DIHYDROCHLORIDE TABLETS

Read this Patient Information before you start taking pramipexole dihydrochloride tablets and each time you get a refill. There may be new information. This information does not take the place of talking with your doctor about your medical condition or your treatment.

What is pramipexole dihydrochloride tablets?

Pramipexole dihydrochloride tablets is a prescription medicine used to treat:

- signs and symptoms of Parkinson’s disease (PD)
- moderate to severe primary Restless Legs Syndrome (RLS)

It is not known if pramipexole dihydrochloride tablets is safe and effective in children.

What should I tell my doctor before taking pramipexole dihydrochloride tablets?

Before taking pramipexole dihydrochloride tablets, tell your doctor if you:

- feel sleepy during the day from a sleep problem other than Restless Legs Syndrome
- have low blood pressure, or if you feel dizzy or faint, especially when getting up from sitting or lying down
- have trouble controlling your muscles (dyskinesia)
- have kidney problems
- drink alcohol. Alcohol can increase the chance that pramipexole dihydrochloride tablets will make you feel sleepy or fall asleep when you should be awake.
- have any other medical conditions
- are pregnant or plan to become pregnant. It is not known if pramipexole dihydrochloride tablets will harm your unborn baby.
- are breastfeeding or plan to breastfeed. It is not known if pramipexole dihydrochloride tablets passes into your breast milk. You and your doctor should decide if you will take pramipexole dihydrochloride tablets or breastfeed. You should not do both.

Tell your doctor about all the medicines you take, includingprescription and non-prescription medicines, vitamins, and herbal supplements.

The combination of pramipexole dihydrochloride tablets and other medicines may affect each other and may cause side effects. Pramipexole dihydrochloride tablets may affect the way other medicines work, and other medicines may affect how pramipexole dihydrochloride tablets works.

Especially tell your doctor if you take:

- medicines called neuroleptics (phenothiazines, butyrophenones, thioxanthenes) or metoclopramide. Pramipexole dihydrochloride tablets may not work as well if you take these medicines.
- extended-release pramipexole (Pramipexole dihydrochloride tablets ER). Pramipexole is the active ingredient in both Pramipexole dihydrochloride tablets and pramipexole dihydrochloride tablets ER. If you are taking pramipexole dihydrochloride tablets ER, you should not take pramipexole dihydrochloride tablets.
- any other medicines that make you sleepy or may increase the effects of pramipexole dihydrochloride tablets, such as cimetidine (Tagamet).

Ask your doctor for a list of these medicines if you are not sure.

Know the medicines you take. Keep a list of them and show it to your doctor and pharmacist when you get a new medicine.

How should I take pramipexole dihydrochloride tablets?

- Take pramipexole dihydrochloride tablets exactly as your doctor tells you to take it.
- Your doctor will tell you how much pramipexole dihydrochloride tablets to take and when to take it. Do not take more or less pramipexole dihydrochloride tablets than your doctor tells you to.
- Your doctor may change your dose if needed.
- Pramipexole dihydrochloride tablets can be taken with or without food. Taking pramipexole dihydrochloride tablets with food may lower your chances of getting nausea.
- If you take more pramipexole dihydrochloride tablets than your doctor recommends, call your doctor or go to the nearest hospital emergency room right away.
- If you miss a dose, do not double your next dose. Skip the dose you missed and take your next regular dose.
- Do notstop taking pramipexole dihydrochloride tablets without talking to your doctor first. If your doctor tells you to stop taking pramipexole dihydrochloride tablets, you should ask your doctor for specific instructions on how to safely discontinue taking pramipexole dihydrochloride tablets. If you stop pramipexole dihydrochloride tablets you may have withdrawal symptoms (see “withdrawal symptoms” under “ What are the possible side effects of pramipexole dihydrochloride tablets?”).

Do not stop taking pramipexole dihydrochloride tablets without talking to your doctor.

What should I avoid while taking pramipexole dihydrochloride tablets?

- Do not drink alcohol while taking pramipexole dihydrochloride tablets. It can increase your chance of having serious side effects. See “What are the possible side effects of pramipexole dihydrochloride tablets?”
- Do not drive a car, operate a machine, or do other dangerous activities until you know how pramipexole dihydrochloride tablets affects you. Sleepiness caused by pramipexole dihydrochloride tablets can happen as late as 1 year after you start your treatment.

What are the possible side effects of pramipexole dihydrochloride tablets?

Pramipexole dihydrochloride tablets may cause serious side effects, including:

- falling asleep during normal daily activities.Pramipexole dihydrochloride tablets may cause you to fall asleep while you are doing daily activities such as driving, talking with other people, or eating.
  - Some people taking the medicine in pramipexole dihydrochloride tablets have had car accidents because they fell asleep while driving.
  - Some patients did not feel sleepy before they fell asleep while driving. You could fall asleep without any warning.
  Tell your doctor right away if you fall asleep while you are doing activities such as talking, eating, driving, or if you feel sleepier than normal for you.

- low blood pressure when you sit or stand up quickly.You may have:•dizziness•nausea•fainting•sweatingSit and stand up slowly after you have been sitting or lying down.

- unusual urges.Some people who take certain medicines to treat Parkinson’s disease or RLS, including pramipexole dihydrochloride tablets, have reported problems, such as gambling, compulsive eating, compulsive buying, and increased sex drive.
  If you or your family members notice that you are developing unusual urges or behaviors, talk to your doctor.
- hallucinations and other psychotic-like behavior(seeing visions, hearing sounds or feeling sensations that are not real, confusion, excessive suspicion, aggressive behavior, agitation, delusional beliefs and disorganized thinking). The chances of having hallucinations or other psychotic-like changes are higher in people taking Pramipexole dihydrochloride tablets for Parkinson’s disease who are elderly (age 65 or older).
  If you have hallucinations or other psychotic-like changes, talk with your doctor right away.
- uncontrolled sudden movements(dyskinesia).
  If you have new dyskinesia or your existing dyskinesia gets worse tell your doctor.
- posture changes.Talk with your doctor if you have posture changes you cannot control. These may include your neck bending forward, bending forward at the waist, or tilting sideways when you sit, stand, or walk.
- withdrawal symptoms.pramipexole dihydrochloride tablets is a dopamine agonist medicine. Dopamine agonist medicines, including pramipexole dihydrochloride tablets, can cause withdrawal symptoms as your dose is slowly lowered (tapered) or when treatment with pramipexole dihydrochloride tablets is stopped. Tell your doctor right away if you get any of the following withdrawal symptoms:
- fever
- confusion
- severe muscle stiffness
- feeling like you do not care about things you usually care about (apathy)
- anxiety
- depression
- fatigue
- insomnia
- sweating
- pain

After you have stopped taking pramipexole dihydrochloride tablets, your doctor may need to restart you at a low dose of pramipexole dihydrochloride tablets if you get severe withdrawal symptoms.

The most common side effects in people taking pramipexole dihydrochloride tablets for Restless Legs Syndrome are nausea and headache.

The most common side effects in people taking pramipexole dihydrochloride tablets for Parkinson’s disease are:

- nausea
- dizziness
- insomnia
- constipation
- muscle weakness
- abnormal dreams
- confusion
- memory problems (amnesia)
- urinating more often than normal

These are not all the possible side effects of pramipexole dihydrochloride tablets. Tell your doctor if you have any side effect that bothers you.

Call your doctor for medical advice about side effects. You may report side effects to FDA at 1-800-FDA-1088.

How should I store pramipexole dihydrochloride tablets?

- Store pramipexole dihydrochloride tablets at 20 ºC to 25ºC (68 ºF to 77ºF); (see USP controlled Room Temperature).
- Keep pramipexole dihydrochloride tablets out of the light.
- Keep pramipexole dihydrochloride tablets and all medicines out of the reach of children.

General Information about the safe and effective use of pramipexole dihydrochloride tablets.

Medicines are sometimes prescribed for purposes other than those listed in a Patient Information leaflet. Do not use pramipexole dihydrochloride tablets for a condition for which it was not prescribed. Do not give pramipexole dihydrochloride tablets to other people, even if they have the same symptoms that you have. It may harm them.

This Patient Information leaflet summarizes the most important information about pramipexole dihydrochloride tablets. If you would like more information, talk with your doctor. You can ask your pharmacist or doctor for information about pramipexole dihydrochloride tablets that is written for healthcare professionals.

For more information, call ScieGen Pharmaceuticals, Inc. at 1-855-724-3436.

What are the ingredients in pramipexole dihydrochloride tablets?

Active Ingredient:pramipexole dihydrochloride USP
Inactive Ingredients:Mannitol, corn starch, colloidal silicon dioxide, povidone and magnesium stearate

This Patient Information has been approved by the U.S. Food and Drug Administration.

The brands listed are trademarks of their respective owners and are not trademarks of ScieGen Pharmaceuticals, Inc. The makers of these brands are not affiliated with and do not endorse ScieGen Pharmaceuticals, Inc., or its products.

Manufactured by:
ScieGen Pharmaceuticals, Inc.
Hauppauge, NY 11788 USA

Rev: 10/2025

Marketed by:
GSMS, Inc.
Camarillo, CA 93012 USA

Package/Label Display Panel

NDC 60429-085-90

PRAMIPEXOLE
DIHYDROCHLORIDE
TABLETS

0.125 mg

PHARMACIST: Dispense the accompanying
Patient Information to each patient.

90 TABLETS Rx Only

NDC 60429-086-90

PRAMIPEXOLE
DIHYDROCHLORIDE
TABLETS

0.25 mg

PHARMACIST: Dispense the accompanying
Patient Information to each patient.

90 TABLETS Rx Only

NDC 60429-087-90

PRAMIPEXOLE
DIHYDROCHLORIDE
TABLETS

0.5 mg

PHARMACIST: Dispense the accompanying
Patient Information to each patient.

90 TABLETS Rx Only

NDC 60429-088-90

PRAMIPEXOLE
DIHYDROCHLORIDE
TABLETS

0.75 mg

PHARMACIST: Dispense the accompanying
Patient Information to each patient.

90 TABLETS Rx Only

NDC 60429-089-90

PRAMIPEXOLE
DIHYDROCHLORIDE
TABLETS

1 mg

PHARMACIST: Dispense the accompanying
Patient Information to each patient.

90 TABLETS Rx Only

NDC 60429-090-90

PRAMIPEXOLE
DIHYDROCHLORIDE
TABLETS

1.5 mg

PHARMACIST: Dispense the accompanying
Patient Information to each patient.

90 TABLETS Rx Only